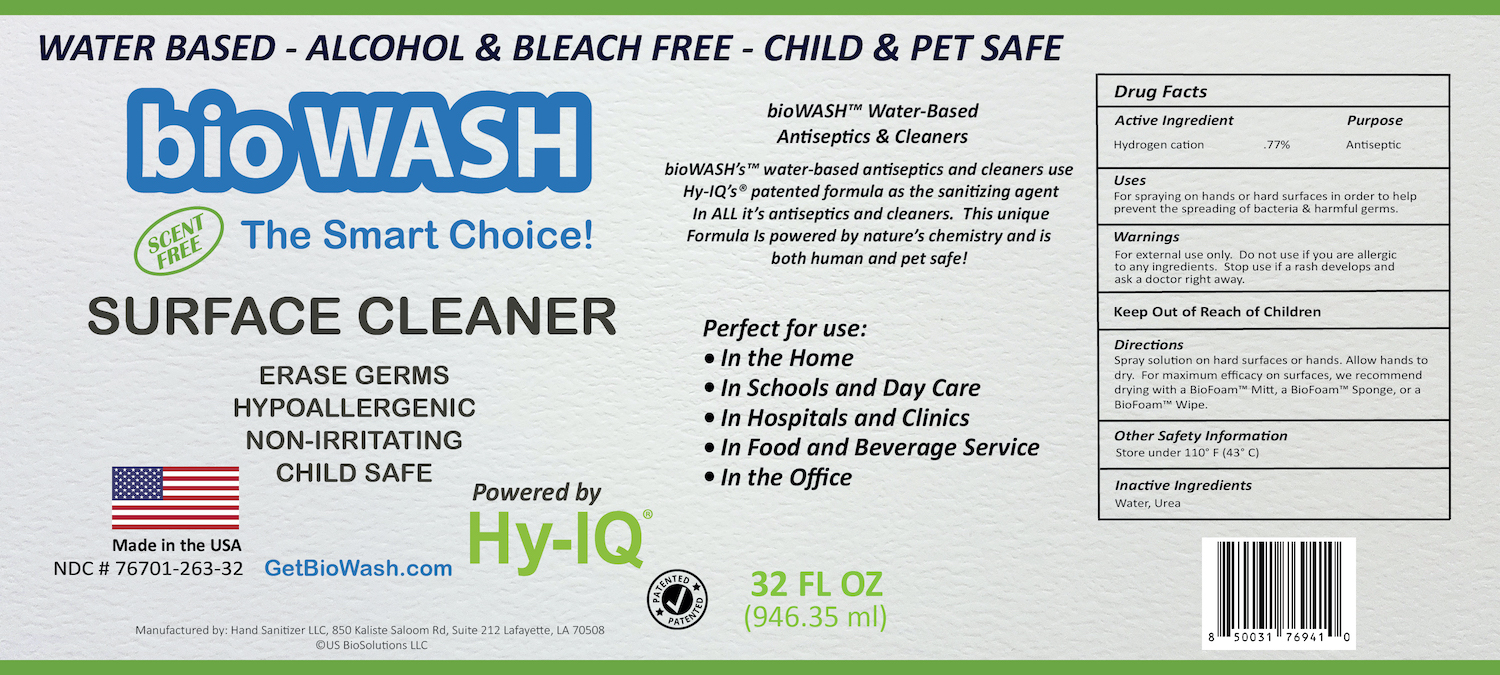 DRUG LABEL: BioWash Surface Cleaner
NDC: 76701-263 | Form: SPRAY
Manufacturer: Hand Sanitizer LLC
Category: otc | Type: HUMAN OTC DRUG LABEL
Date: 20210821

ACTIVE INGREDIENTS: HYDROGEN CATION 10 mg/1 mL
INACTIVE INGREDIENTS: UREA 50 mg/1 mL; WATER 940 mg/1 mL

BioWash Surface Cleaner

Active Ingredient

Hydrogen Cation .77%

Purpose

Antiseptic

Uses

For spraying on hands or hard surfaces in order to prevent the spreading of bacteria and harmful germs.

Warnings

For external use only. Do not use if you are allergic to any ingredients. Stop use if rash develops and ask a doctor right away.

Keep Out of Reach of Children

Directions

Spray solution on hard surfaces or hands. Allow hands to dry. For maximum efficacy on surfaces, we recommend drying with a BioFoam™ Mitt, a BioFoam™ Sponge, or a BioFoam™ Wipe.

Other Safety Information

Store under 110º F (43º C)

Inactive Ingredients

Water, Urea